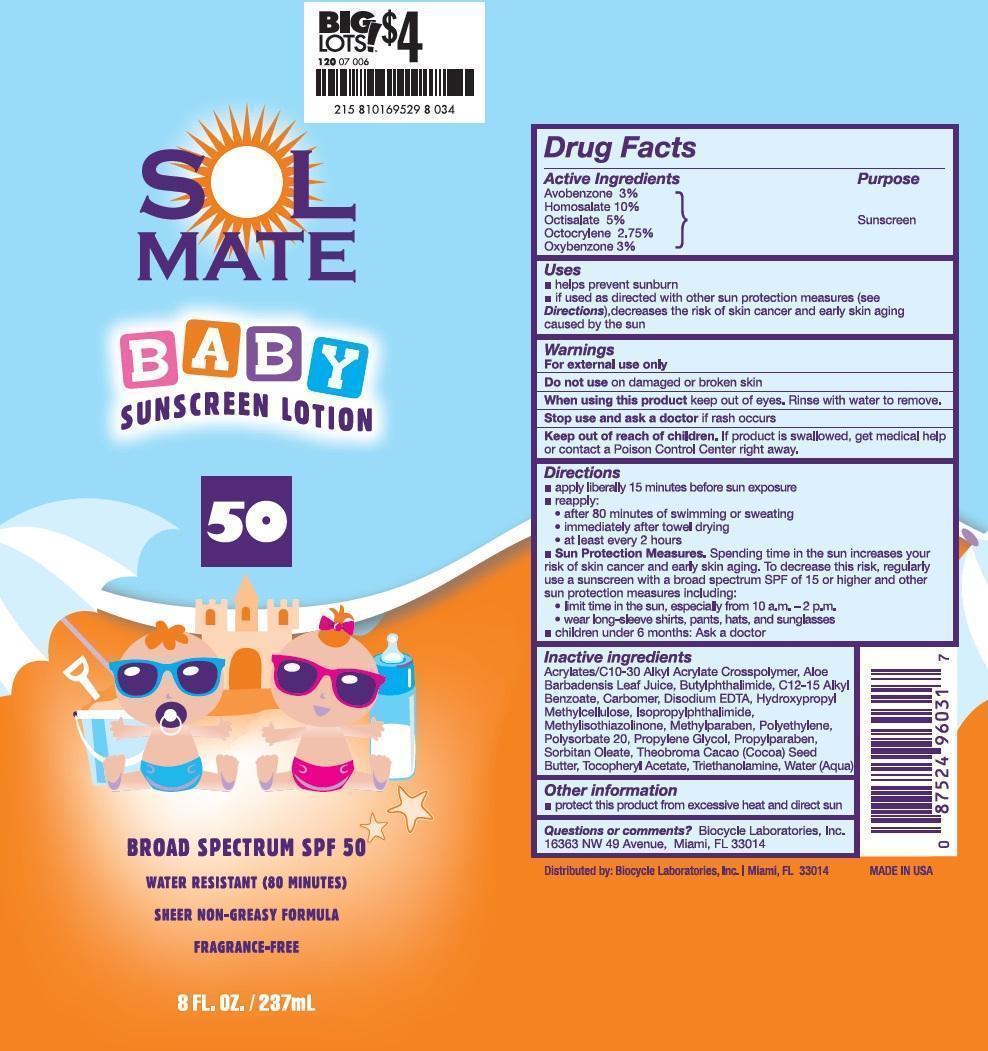 DRUG LABEL: SolMate
NDC: 58443-0140 | Form: LOTION
Manufacturer: Prime Enterprises, Inc.
Category: otc | Type: HUMAN OTC DRUG LABEL
Date: 20200117

ACTIVE INGREDIENTS: AVOBENZONE 29.7 mg/1 mL; HOMOSALATE 99 mg/1 mL; OCTISALATE 49.5 mg/1 mL; OCTOCRYLENE 27.225 mg/1 mL; OXYBENZONE 29.7 mg/1 mL
INACTIVE INGREDIENTS: (C10-C30)ALKYL METHACRYLATE ESTER; ALOE VERA LEAF; N-BUTYLPHTHALIMIDE; ISOPROPYLPHTHALIMIDE; ALKYL (C12-15) BENZOATE; CARBOMER HOMOPOLYMER TYPE C (ALLYL PENTAERYTHRITOL CROSSLINKED); EDETATE DISODIUM; HYPROMELLOSES; METHYLPARABEN; HIGH DENSITY POLYETHYLENE; POLYSORBATE 20; PROPYLENE GLYCOL; PROPYLPARABEN; SORBITAN MONOOLEATE; COCOA BUTTER; .ALPHA.-TOCOPHEROL ACETATE; TROLAMINE; METHYLISOTHIAZOLINONE; WATER

Active Ingredients

Avobenzone 3 %, Homosalate 10 %, Octisalate 5 %, Octocrylene 2.75 %, and Oxybenzone 3 %

Purpose

Sunscreen

Uses

- helps prevent sunburn
- if used as directed with other sun protection measures (see Dictections), decreases the risk of skin cancer and early skin aging caused by the sun

Warnings

OTHER SAFETY INFORMATION

For external use only

Do not use on damaged or broken skin

When using this product keep out of eyes. Rinse with water to remove.

Stop use and ask a doctor if rash occurs

Keep out of reach of children. If product is swallowed, get medical help or contact a Poison Control Center right away.

Directions

- apply liberally 15 minutes before sun exposure
- reapply:

- after 80 minutes of swimming or sweating
- immediately after towel drying
- at least every 2 hours

- Sun Protection Measures. Spending time in the sun increases your risk of skin cancer and early skin aging. To decrease this risk, regularly use a sunscreen with a broad spectrum SPF of 15 or higher and other sun protection measures including:
- limit time in the sun especially from 10 a.m. – 2 p.m.
- wear long-sleeve shirts, pants, hats, and sunglasses

- children under 6 months: Ask a doctor

Inactive Ingredients

Acrylates/C10-30 Alkyl Acrylate Crosspolymer, Aloe Barbadensis Leaf Juice, Butylphthalimide, C12-15 Alkyl Benzoate, Carbomer, Disodium EDTA, Fragrance, Hydroxypropyl Methylcellulose, Isopropylphthalimide, Methylisothiazolinone, Methylparaben, Polyethylene, Polysorbate 20, Propylene Glycol, Propylparaben, Sorbitan Oleate, Theobroma Cacao (Cocoa) Seed Butter, Tocopheryl Acetate, Triethanolamine, Water

Other information

- protect this product from excesive heat and direct sun

Questions or Comments?: Biocycle Laboratories, Inc.

16363 NW 49 Avenue, Miami, FL 33014

PRINCIPAL DISPLAY PANEL - 237 mL Bottle Label

SOL

MATE

BABY

SUNSCREEN LOTION

50

BROAD SPECTRUM SPF 50

WATER RESISTANT (80 MINUTES)

SHEER NON-GREASY FORMULA

FRAGRANCE FREE

8 FL.OZ./237mL